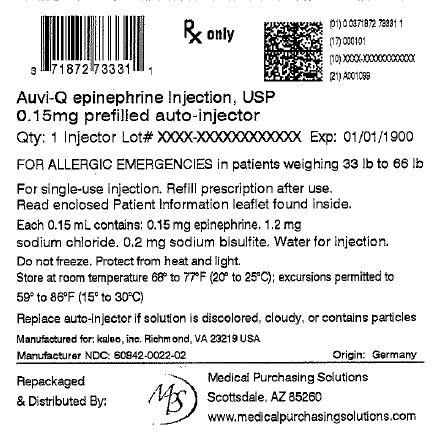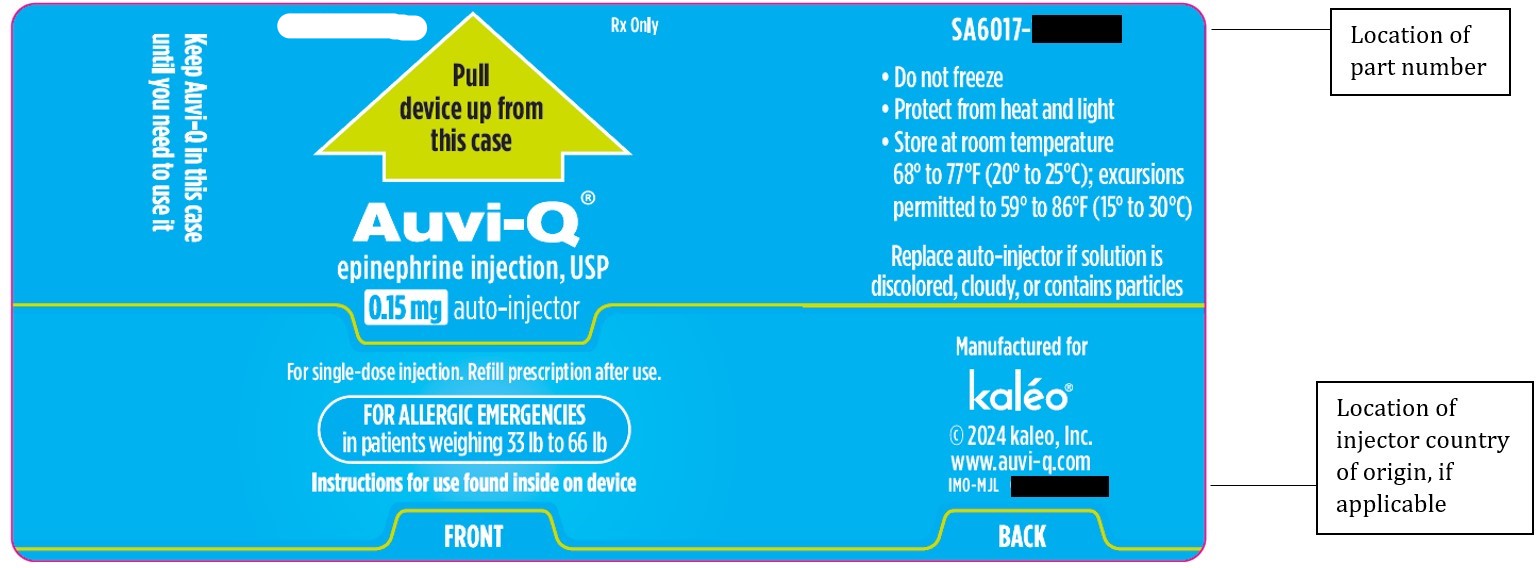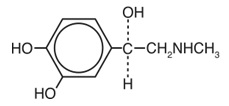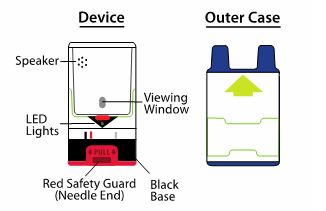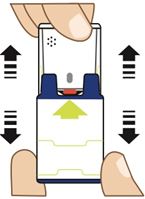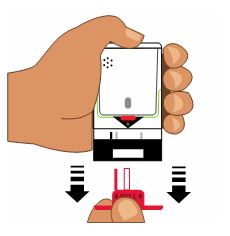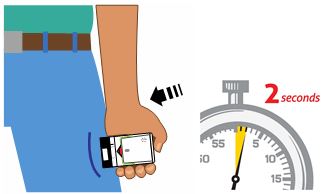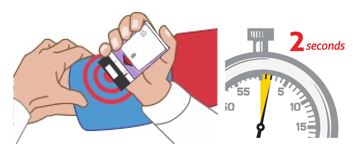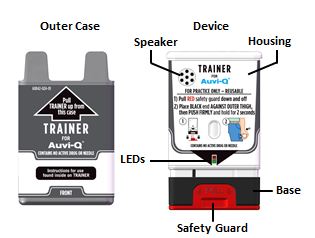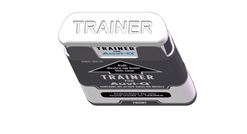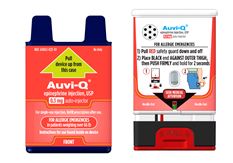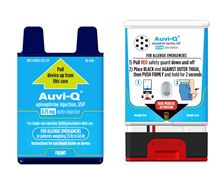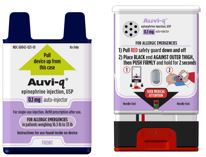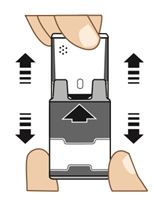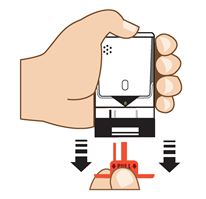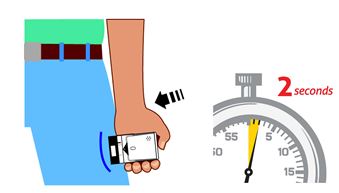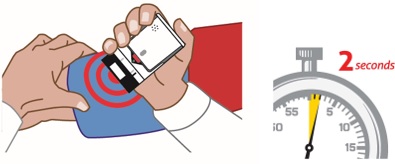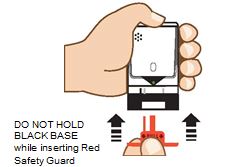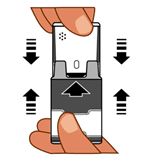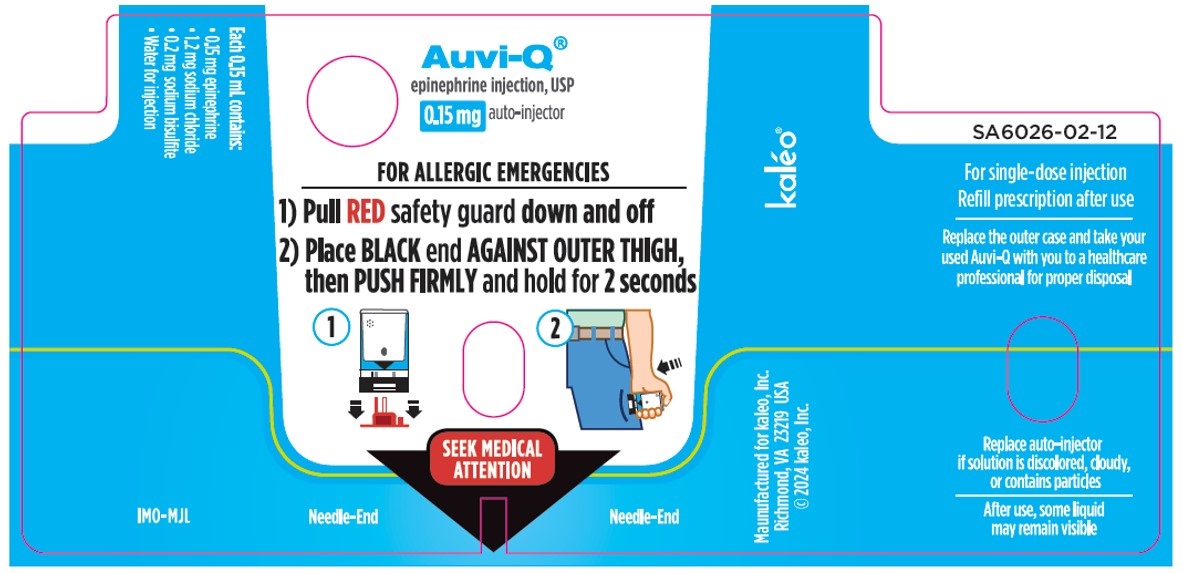 DRUG LABEL: Auvi-Q
NDC: 71872-7333 | Form: INJECTION, SOLUTION
Manufacturer: Medical Purchasing Solutions, LLC
Category: prescription | Type: HUMAN PRESCRIPTION DRUG LABEL
Date: 20241216

ACTIVE INGREDIENTS: EPINEPHRINE 0.15 mg/0.15 mL
INACTIVE INGREDIENTS: SODIUM CHLORIDE 1.2 mg/0.15 mL; SODIUM BISULFITE 0.2 mg/0.15 mL; WATER; HYDROCHLORIC ACID

HIGHLIGHTS OF PRESCRIBING INFORMATION

These highlights do not include all the information needed to use AUVI-Q® safely and effectively. See full prescribing information for AUVI-Q.
AUVI-Q® (epinephrine injection, USP),
for intramuscular or subcutaneous use
Initial U.S. Approval: 1939

1 INDICATIONS AND USAGE

AUVI-Q is a non-selective alpha and beta-adrenergic receptor agonist indicated in the emergency treatment of allergic reactions (Type I) including anaphylaxis. (1)

2 DOSAGE AND ADMINISTRATION

- Patients greater than or equal to 30 kg (66 lbs): AUVI-Q 0.3 mg (2)
- Patients 15 to 30 kg (33 to 66 lbs): AUVI-Q 0.15 mg (2)
- Patients 7.5 to 15 kg (16.5 to 33 lbs): AUVI-Q 0.1 mg (2)

Inject AUVI-Q intramuscularly or subcutaneously into the anterolateral aspect of the thigh, through clothing if necessary. Each device is a single-dose injection. (2)

3 DOSAGE FORMS AND STRENGTHS

Injection:

- 0.3 mg: 0.3 mg/0.3 mL epinephrine injection, USP, pre-filled autoinjector (3)
- 0.15 mg: 0.15 mg/0.15 mL epinephrine injection, USP, pre-filled autoinjector (3)
- 0.1 mg: 0.1 mg/0.1 mL epinephrine injection, USP, pre-filled autoinjector (3)

4 CONTRAINDICATIONS

None. (4)

5 WARNINGS AND PRECAUTIONS

- In conjunction with use, seek immediate medical or hospital care. (5.1)
- Do not inject intravenously, into buttock, or into digits, hands, or feet. (5.2)
- To minimize the risk of injection-related injury, instruct caregivers to hold the child’s leg firmly in place and limit movement prior to and during injection when administering to young children or infants. (5.2)
- Rare cases of serious skin and soft tissue infections have been reported following epinephrine injection. Advise patients to seek medical care if they develop signs or symptoms of infection at the epinephrine injection site. (5.3)
- The presence of a sulfite in this product should not deter use. (5.4)
- Administer with caution in patients with heart disease; may aggravate angina pectoris or produce ventricular arrhythmias. (5.5)

6 ADVERSE REACTIONS

Adverse reactions to epinephrine include anxiety, apprehensiveness, restlessness, tremor, weakness, dizziness, sweating, palpitations, pallor, nausea and vomiting, headache, and/or respiratory difficulties. (6)

To report SUSPECTED ADVERSE REACTIONS, contact kaleo, Inc. at 1-877-302-8847 or FDA at 1-800-FDA-1088 or www.fda.gov/medwatch.

7 DRUG INTERACTIONS

- Cardiac glycosides or diuretics: observe for development of cardiac arrhythmias. (7)
- Tricyclic antidepressants, monoamine oxidase inhibitors, levothyroxine sodium, and certain antihistamines: potentiate effects of epinephrine. (7)
- Beta-adrenergic blocking drugs: antagonize cardiostimulating and bronchodilating effects of epinephrine. (7)
- Alpha-adrenergic blocking drugs: antagonize vasoconstricting and hypertensive effects of epinephrine. (7)
- Ergot alkaloids: may reverse the pressor effects of epinephrine. (7)

8 USE IN SPECIFIC POPULATIONS

- Elderly patients may be at greater risk of developing adverse reactions. (5.5, 8.5)

FULL PRESCRIBING INFORMATION

1 INDICATIONS AND USAGE

AUVI-Q® is indicated in the emergency treatment of allergic reactions (Type I) including anaphylaxis to stinging insects (e.g., order Hymenoptera, which include bees, wasps, hornets, yellow jackets and fire ants) and biting insects (e.g., triatoma, mosquitoes), allergen immunotherapy, foods, drugs, diagnostic testing substances (e.g., radiocontrast media) and other allergens, as well as idiopathic anaphylaxis or exercise-induced anaphylaxis.

AUVI-Q is intended for immediate administration in patients who are determined to be at increased risk for anaphylaxis, including individuals with a history of anaphylactic reactions.

Anaphylactic reactions may occur within minutes after exposure and consist of flushing, apprehension, syncope, tachycardia, thready or unobtainable pulse associated with a fall in blood pressure, convulsions, vomiting, diarrhea and abdominal cramps, involuntary voiding, wheezing, dyspnea due to laryngeal spasm, pruritus, rashes, urticaria or angioedema.

AUVI-Q is intended for immediate self-administration as emergency supportive therapy only and is not a substitute for immediate medical care.

2 DOSAGE AND ADMINISTRATION

Selection of the appropriate dosage strength (AUVI-Q 0.3 mg, AUVI-Q 0.15 mg or AUVI-Q 0.1 mg) is determined according to patient body weight.

- Patients greater than or equal to 30 kg (approximately 66 pounds or more): AUVI-Q 0.3 mg
- Patients 15 to 30 kg (33 to 66 pounds): AUVI-Q 0.15 mg
- Patients 7.5 to 15 kg (16.5 to 33 pounds): AUVI-Q 0.1 mg

Inject AUVI-Q intramuscularly or subcutaneously into the anterolateral aspect of the thigh, through clothing if necessary. Instruct caregivers of young children and infants who are prescribed AUVI-Q and who may be uncooperative and kick or move during an injection to hold the child’s leg firmly in place and limit movement prior to and during an injection [see Warnings and Precautions (5.2)] .

Each AUVI-Q contains a single dose of epinephrine for single-dose injection. Since the doses of epinephrine delivered from AUVI-Q are fixed, consider using other forms of injectable epinephrine if doses lower than 0.1 mg are deemed necessary.

The prescriber should carefully assess each patient to determine the most appropriate dose of epinephrine, recognizing the life-threatening nature of the reactions for which this drug is indicated. With severe persistent anaphylaxis, repeat injections with an additional AUVI-Q may be necessary. More than two sequential doses of epinephrine should only be administered under direct medical supervision [see Warnings and Precautions (5.1)] .

The epinephrine solution in the viewing window of AUVI-Q should be inspected visually for particulate matter and discoloration. Epinephrine is light sensitive and should be stored in the outer case provided to protect it from light [see How Supplied/ Storage and Handling (16)] .

3 DOSAGE FORMS AND STRENGTHS

Injection:

- 0.3 mg/0.3 mL epinephrine injection, USP, pre-filled autoinjector
- 0.15 mg/0.15 mL epinephrine injection, USP, pre-filled autoinjector
- 0.1 mg/0.1 mL epinephrine injection, USP, pre-filled autoinjector

4 CONTRAINDICATIONS

None.

5 WARNINGS AND PRECAUTIONS

5.1 Emergency Treatment

AUVI-Q is not intended as a substitute for immediate medical care. In conjunction with the administration of epinephrine, the patient should seek immediate medical or hospital care.More than two sequential doses of epinephrine should only be administered under direct medical supervision [see Indications and Usage (1), Dosage and Administration (2) and Patient Counseling Information (17)] .

5.2 Injection-Related Complications

AUVI-Q should ONLYbe injected into the anterolateral aspect of the thigh [see Dosage and Administration (2) and Patient Counseling Information (17)] .

- Do not inject intravenously.Large doses or accidental intravenous injection of epinephrine may result in cerebral hemorrhage due to sharp rise in blood pressure. Rapidly acting vasodilators can counteract the marked pressor effects of epinephrine if there is such inadvertent administration.
- Do not inject into buttock.Injection into the buttock may not provide effective treatment of anaphylaxis. Advise the patient to go immediately to the nearest emergency room for further treatment of anaphylaxis. Additionally, injection into the buttock has been associated with Clostridial infections (gas gangrene). Cleansing with alcohol does not kill bacterial spores, and therefore, does not lower this risk.
- Do not inject into digits, hands or feet.Since epinephrine is a strong vasoconstrictor, accidental injection into the digits, hands or feet may result in loss of blood flow to the affected area. Advise the patient to go immediately to the nearest emergency room and to inform the healthcare provider in the emergency room of the location of the accidental injection. Treatment of such inadvertent administration should consist of vasodilation, in addition to further appropriate treatment of anaphylaxis [see Adverse Reactions (6)] .
- Hold leg firmly during injection.To minimize the risk of injection-related injury when administering AUVI-Q to young children or infants, instruct caregivers to hold the child’s leg firmly in place and limit movement prior to and during injection.

5.3 Serious Infections at the Injection Site

Rare cases of serious skin and soft tissue infections, including necrotizing fasciitis and myonecrosis caused by Clostridia (gas gangrene), have been reported at the injection site following epinephrine injection for anaphylaxis. Clostridiumspores can be present on the skin and introduced into the deep tissue with subcutaneous or intramuscular injection. While cleansing with alcohol may reduce the presence of bacteria on the skin, alcohol cleansing does not kill Clostridiumspores. To decrease the potential risk of a rare, but serious Clostridiuminfection, do not inject AUVI-Q into the buttock [see Warnings and Precautions (5.2)] . Advise patients to seek medical care if they develop signs or symptoms of infection, such as persistent redness, warmth, swelling, or tenderness, at the epinephrine injection site.

5.4 Allergic Reactions Associated with Sulfite

Epinephrine is the preferred treatment for serious allergic reactions or other emergency situations even though this product contains sodium bisulfite, a sulfite that may, in other products, cause allergic-type reactions including anaphylactic symptoms or life-threatening or less severe asthmatic episodes in certain susceptible persons.

The presence of a sulfite in this product should not deter administration of the drug for treatment of serious allergic or other emergency situations even if the patient is sulfite-sensitive.

The alternatives to using epinephrine in a life-threatening situation may not be satisfactory.

5.5 Disease Interactions

Some patients may be at greater risk for developing adverse reactions after epinephrine administration. Despite these concerns, it should be recognized that the presence of these conditions is not a contraindication to epinephrine administration in an acute, life-threatening situation. Therefore, patients with these conditions, and/or any other person who might be in a position to administer AUVI-Q to a patient experiencing anaphylaxis should be carefully instructed in regard to the circumstances under which epinephrine should be used.

- Patients with Heart Disease

Epinephrine should be administered with caution to patients who have heart disease, including patients with cardiac arrhythmias, coronary artery or organic heart disease, or hypertension. In such patients, or in patients who are on drugs that may sensitize the heart to arrhythmias, epinephrine may precipitate or aggravate angina pectoris as well as produce ventricular arrhythmias [see Drug Interactions (7) and Adverse Reactions (6)] .

- Other Patients and Diseases

Epinephrine should be administered with caution to patients with hyperthyroidism, diabetes, elderly individuals, and pregnant women. Patients with Parkinson’s disease may notice a temporary worsening of symptoms.

6 ADVERSE REACTIONS

Due to lack of randomized, controlled clinical trials of epinephrine for the treatment of anaphylaxis, the true incidence of adverse reactions associated with the systemic use of epinephrine is difficult to determine. Adverse reactions reported in observational trials, case reports, and studies are listed below.

Common adverse reactions to systemically administered epinephrine include anxiety; apprehensiveness; restlessness; tremor; weakness; dizziness; sweating; palpitations; pallor; nausea and vomiting; headache; and/or respiratory difficulties. These symptoms occur in some persons receiving therapeutic doses of epinephrine, but are more likely to occur in patients with hypertension or hyperthyroidism [see Warnings and Precautions (5.5)] .

Arrhythmias, including fatal ventricular fibrillation, have been reported, particularly in patients with underlying cardiac disease or those receiving certain drugs [see Warnings and Precautions (5.5) and Drug Interactions (7)] .

Rapid rises in blood pressure have produced cerebral hemorrhage, particularly in elderly patients with cardiovascular disease [see Warnings and Precautions (5.5)] .

Angina may occur in patients with coronary artery disease [see Warnings and Precautions (5.5)] .

Rare cases of stress cardiomyopathy have been reported in patients treated with epinephrine.

Accidental injection into the digits, hands or feet may result in loss of blood flow to the affected area [see Warnings and Precautions (5.2)] .

Adverse events experienced as a result of accidental injections may include increased heart rate, local reactions including injection site pallor, coldness and hypoesthesia or injury at the injection site resulting in bruising, bleeding, discoloration, erythema or skeletal injury.

Injection of epinephrine into the buttock has resulted in cases of gas gangrene [see Warnings and Precautions (5.2)] .

Rare cases of serious skin and soft tissue infections, including necrotizing fasciitis and myonecrosis caused by Clostridia (gas gangrene), have been reported at the injection site following epinephrine injection in the thigh [see Warnings and Precautions (5.2)] .

7 DRUG INTERACTIONS

7.1 Drugs Increasing Risk of Cardiac Arrhythmias

Patients who receive epinephrine while concomitantly taking cardiac glycosides, diuretics, or anti-arrhythmics should be observed carefully for the development of cardiac arrhythmias [see Warnings and Precautions (5.5)] .

7.2 Drugs Potentiating Effects of Epinephrine

The effects of epinephrine may be potentiated by tricyclic antidepressants, monoamine oxidase inhibitors, levothyroxine sodium, and certain antihistamines, notably chlorpheniramine, tripelennamine, and diphenhydramine.

7.3 Drugs Antagonizing Effects of Epinephrine

The cardiostimulating and bronchodilating effects of epinephrine are antagonized by beta-adrenergic blocking drugs, such as propranolol.

The vasoconstricting and hypertensive effects of epinephrine are antagonized by alpha-adrenergic blocking drugs, such as phentolamine.

Ergot alkaloids may also reverse the pressor effects of epinephrine.

8 USE IN SPECIFIC POPULATIONS

8.1 Pregnancy

Risk Summary

There are no adequate and well controlled studies of the acute effect of epinephrine in pregnant women. In animal reproductive studies, epinephrine administered by the subcutaneous route to rabbits, mice, and hamsters during the period of organogenesis was teratogenic at doses 7 times and higher than the maximum recommended human intramuscular and subcutaneous dose on a mg/m^2basis. Epinephrine is the first-line medication of choice for the treatment of anaphylaxis during pregnancy in humans. Epinephrine should be used for treatment of anaphylaxis during pregnancy in the same manner as it is used in non-pregnant patients.

In the U.S. general population, the estimated background risk of major birth defects and miscarriage in clinically recognized pregnancies is 2 to 4% and 15 to 20%, respectively.

Clinical Considerations

Disease-associated maternal and embryo/fetal risk:

During pregnancy, anaphylaxis can be catastrophic and can lead to hypoxic-ischemic encephalopathy and permanent central nervous system damage or death in the mother and, more commonly, in the fetus or neonate. The prevalence of anaphylaxis occurring during pregnancy is reported to be approximately 3 cases per 100,000 deliveries.

Management of anaphylaxis during pregnancy is similar to management in the general population. Epinephrine is the first line-medication of choice for treatment of anaphylaxis; it should be used in the same manner in pregnant and non-pregnant patients. In conjunction with the administration of epinephrine, the patient should seek immediate medical or hospital care.

Data

Animal Data:

In an embryofetal development study with rabbits dosed during the period of organogenesis, epinephrine was shown to be teratogenic (including gastroschisis and embryonic lethality) at doses approximately 40 times the maximum recommended intramuscular or subcutaneous dose (on a mg/m^2basis at a maternal subcutaneous dose of 1.2 mg/kg/day for two to three days).

In an embryofetal development study with mice dosed during the period of organogenesis, epinephrine was shown to be teratogenic (including embryonic lethality) at doses approximately 8 times the maximum recommended intramuscular or subcutaneous dose (on a mg/m^2basis at a maternal subcutaneous dose of 1 mg/kg/day for 10 days). These effects were not seen in mice at approximately 4 times the maximum recommended daily intramuscular or subcutaneous dose (on a mg/m^2basis at a subcutaneous maternal dose of 0.5 mg/kg/day for 10 days).

In an embryofetal development study with hamsters dosed during the period of organogenesis from gestation days 7 to 10, epinephrine was shown to be teratogenic at doses approximately 7 times the maximum recommended daily intramuscular or subcutaneous dose (on a mg/m^2basis at a maternal subcutaneous dose of 0.5 mg/kg/day for 4 days).

8.2 Lactation

Risk Summary

There is no information on the presence of epinephrine in human milk, the effects on breastfed infants, or the effects on milk production. Epinephrine is the first line-medication of choice for treatment of anaphylaxis; it should be used in the same manner in breastfeeding and non-breastfeeding patients.

8.4 Pediatric Use

AUVI-Q may be administered to pediatric patients at a dosage appropriate to body weight [see Dosage and Administration (2)] . Clinical experience with the use of epinephrine suggests that the adverse reactions seen in children are similar in nature and extent to those both expected and reported in adults. Since the doses of epinephrine delivered from AUVI-Q are fixed, consider using other forms of injectable epinephrine if doses lower than 0.1 mg are deemed necessary.

8.5 Geriatric Use

Clinical studies of AUVI-Q did not include sufficient numbers of subjects aged 65 and over to determine whether they respond differently from younger subjects. Other reported clinical experience has not identified differences in responses between the elderly and younger patients. Epinephrine should be administered with caution in elderly individuals, who may be at greater risk for developing adverse reactions after epinephrine administration [see Warnings and Precautions (5.5), Overdosage (10)] .

10 OVERDOSAGE

Overdosage of epinephrine may produce extremely elevated arterial pressure, which may result in cerebrovascular hemorrhage, particularly in elderly patients. Overdosage may also result in pulmonary edema because of peripheral vascular constriction together with cardiac stimulation. Treatment consists of rapidly acting vasodilators or alpha-adrenergic blocking drugs and/or respiratory support.

Epinephrine overdosage can also cause transient bradycardia followed by tachycardia, and these may be accompanied by potentially fatal cardiac arrhythmias. Premature ventricular contractions may appear within one minute after injection and may be followed by multifocal ventricular tachycardia (prefibrillation rhythm). Subsidence of the ventricular effects may be followed by atrial tachycardia and occasionally by atrioventricular block. Treatment of arrhythmias consists of administration of a beta-adrenergic blocking drug such as propranolol.

Overdosage sometimes results in extreme pallor and coldness of the skin, metabolic acidosis, and kidney failure. Suitable corrective measures must be taken in such situations.

11 DESCRIPTION

AUVI-Q (epinephrine injection, USP) 0.3 mg, 0.15 mg and 0.1 mg is an autoinjector and a combination product containing drug and device components.

AUVI-Q includes audible (electronic voice instructions, beeps) and visible (LED lights) cues for use. The needle automatically retracts after the injection is complete.

Each AUVI-Q 0.3 mg delivers a single dose of 0.3 mg epinephrine from epinephrine injection, USP (0.3 mL) in a sterile solution.

Each AUVI-Q 0.15 mg delivers a single dose of 0.15 mg epinephrine from epinephrine injection, USP (0.15 mL) in a sterile solution.

Each AUVI-Q 0.1 mg delivers a single dose of 0.1 mg epinephrine from epinephrine injection, USP (0.1 mL) in a sterile solution .

AUVI-Q 0.3 mg, AUVI-Q 0.15 mg and AUVI-Q 0.1 mg each contain 0.76 mL epinephrine solution. 0.3 mL, 0.15 mL and 0.1 mL epinephrine solution is dispensed for AUVI-Q 0.3 mg, AUVI-Q 0.15 mg and AUVI-Q 0.1 mg, respectively, when activated. The remaining solution is not available for future use and should be discarded.

Each 0.3 mL in AUVI-Q 0.3 mg contains 0.3 mg epinephrine, 2.3 mg sodium chloride, 0.5 mg sodium bisulfite, hydrochloric acid to adjust pH, and water for injection. The pH range is 2.2–5.0.

Each 0.15 mL in AUVI-Q 0.15 mg contains 0.15 mg epinephrine, 1.2 mg sodium chloride, 0.2 mg sodium bisulfite, hydrochloric acid to adjust pH, and water for injection. The pH range is 2.2–5.0.

Each 0.1 mL in AUVI-Q 0.1 mg contains 0.1 mg epinephrine, 0.78 mg sodium chloride, 0.15 mg sodium bisulfite, hydrochloric acid to adjust pH, and water for injection. The pH range is 2.2–5.0.

Epinephrine is a sympathomimetic catecholamine. Chemically, epinephrine is (-)-3,4-Dihydroxy-α-[(methylamino)methyl]benzyl alcohol with the following structure:

Epinephrine solution deteriorates rapidly on exposure to air or light, turning pink from oxidation to adrenochrome and brown from the formation of melanin.

AUVI-Q is not made with natural rubber latex.

AUVI-Q instructional and safety systems should be thoroughly reviewed with patients and caregivers prior to use [see Patient Counseling Information (17)] .

12 CLINICAL PHARMACOLOGY

12.1 Mechanism of Action

Epinephrine acts on both alpha and beta-adrenergic receptors.

12.2 Pharmacodynamics

Through its action on alpha-adrenergic receptors, epinephrine lessens the vasodilation and increased vascular permeability that occurs during anaphylaxis, which can lead to loss of intravascular fluid volume and hypotension.

Through its action on beta-adrenergic receptors, epinephrine causes bronchial smooth muscle relaxation and helps alleviate bronchospasm, wheezing and dyspnea that may occur during anaphylaxis.

Epinephrine also alleviates pruritus, urticaria, and angioedema and may relieve gastrointestinal and genitourinary symptoms associated with anaphylaxis because of its relaxer effects on the smooth muscle of the stomach, intestine, uterus and urinary bladder.

When given subcutaneously or intramuscularly, epinephrine has a rapid onset and short duration of action.

13 NONCLINICAL TOXICOLOGY

13.1 Carcinogenesis, Mutagenesis, Impairment of Fertility

Long-term studies to evaluate the carcinogenic potential of epinephrine have not been conducted.

Epinephrine and other catecholamines have been shown to have mutagenic potential in vitro. Epinephrine was positive in the Salmonellabacterial reverse mutation assay, positive in the mouse lymphoma assay, and negative in the in vivomicronucleus assay. Epinephrine is an oxidative mutagen based on the E. coliWP2 Mutoxitest bacterial reverse mutation assay. This should not prevent the use of epinephrine under the conditions noted under the Indications and Usage (1) .

The potential for epinephrine to impair reproductive performance has not been evaluated, but epinephrine has been shown to decrease implantation in female rabbits dosed subcutaneously with 1.2 mg/kg/day (40-fold the highest human intramuscular or subcutaneous daily dose) during gestation days 3 to 9.

16 HOW SUPPLIED/STORAGE AND HANDLING

How Supplied

AUVI-Q (epinephrine injection) is available as an autoinjector as described in Table 1.

Table 1 AUVI-Q Autoinjector Package Configurations and Strengths

Package Configuration | Strength | National Drug Code (NDC)
2 autoinjectors | 0.3 mg | NDC 60842-023-02
2 autoinjectors | 0.15 mg | NDC 60842-022-02
2 autoinjectors | 0.1 mg | NDC 60842-021-02

Storage and Handling

Epinephrine is light sensitive and should be stored in the outer case provided to protect it from light. Store at 20℃ to 25℃ (68℉ to 77℉); excursions permitted to 15℃ to 30℃℉ (59℉ to 86℉) [See USP Controlled Room Temperature]. Do not freeze. Before using, check to make sure the solution in the autoinjector is clear and colorless. Replace the autoinjector if the solution is discolored, cloudy, or contains particles.

17 PATIENT COUNSELING INFORMATION

Advise the patient to read the FDA-approved patient labeling (Patient Information and Instructions for Use).

A healthcare provider should review the patient instructions and operation of AUVI-Q, in detail, with the patient or caregiver.

Epinephrine is essential for the treatment of anaphylaxis. Patients who are at risk of or with a history of severe allergic reactions (anaphylaxis) to insect stings or bites, foods, drugs, and other allergens, as well as idiopathic and exercise-induced anaphylaxis, should be carefully instructed about the circumstances under which epinephrine should be used.

Administration and Training

Instruct patients and/or caregivers in the appropriate use of AUVI-Q. AUVI-Q should be injected into the middle of the outer thigh (through clothing, if necessary). Each device is a single-dose injection. Advise patients to seek immediate medical care in conjunction with administration of AUVI-Q.

Young children or infants may be uncooperative and kick or move during an injection. Instruct caregivers to hold the leg of young children or infants firmly in place and limit movement prior to and during injection [see Warnings and Precautions (5.2)] .

Complete patient information, including dosage, directions for proper administration and precautions can be found inside each AUVI-Q carton. Review AUVI-Q’s instructional and safety systems with patients and/or caregivers. These systems include the printed label on the surface of AUVI-Q showing instructions for use and a diagram depicting the injection process, an automatic needle retraction system, visual prompts, electronic beeps, and voice instructions for use. Instruct patients and/or caregivers that the needle will not be visible after the injection and they may not feel the injection when it occurs. Instruct patients that AUVI-Q includes a 2-second countdown after it is activated and then the voice instructions will indicate the injection is complete and to seek emergency medical attention. Instruct patients that AUVI-Q’s black base will lock up onto the device housing and the lights will blink red after the injection is complete. These post-use indicators help patients and/or caregivers know that AUVI-Q has been activated and an epinephrine injection administered.

Instruct patients and/or caregivers to use and practice with the Trainer to familiarize themselves with the use of AUVI-Q in an allergic emergency. The Trainer may be used multiple times.

Adverse Reactions

Epinephrine may produce symptoms and signs that include an increase in heart rate, the sensation of a more forceful heartbeat, palpitations, sweating, nausea and vomiting, difficulty breathing, pallor, dizziness, weakness or shakiness, headache, apprehension, nervousness, or anxiety. These symptoms and signs usually subside rapidly, especially with rest, quiet and recumbency. Patients with hypertension or hyperthyroidism may develop more severe or persistent effects, and patients with coronary artery disease could experience angina. Patients with diabetes may develop increased blood glucose levels following epinephrine administration. Patients with Parkinson’s disease may notice a temporary worsening of symptoms [see Warnings and Precautions (5.5)] .

Accidental Injection

Patients should be advised to seek immediate medical care in the case of accidental injection. Since epinephrine is a strong vasoconstrictor when injected into the digits, hands, or feet, treatment should be directed at vasodilatation if there is such an accidental injection to these areas [see Warnings and Precautions (5.2)] .

Serious Infections at the Injection Site

Rare cases of serious skin and soft tissue infections, including necrotizing fasciitis and myonecrosis caused by Clostridia (gas gangrene), have been reported at the injection site following epinephrine injection for anaphylaxis. Advise patients to seek medical care if they develop signs or symptoms of infection, such as persistent redness, warmth, swelling, or tenderness, at the epinephrine injection site [see Warnings and Precautions (5.3)] .

Storage and Handling

Patients should be instructed to inspect the epinephrine solution visually through the viewing window periodically. AUVI-Q should be replaced if the epinephrine solution appears discolored (pinkish color or darker than slightly yellow), cloudy, or contains particles. Epinephrine is light sensitive and should be stored in the outer case provided to protect it from light. Instruct patients that AUVI-Q must be used or properly disposed once the red safety guard is removed [see How Supplied/ Storage and Handling (16)] .

Complete patient information, including dosage, directions for proper administration and precautions can be found inside each AUVI-Q carton.

Manufactured for:
kaleo, Inc.
Richmond, VA 23219 USA
This product may be covered by one or more U.S. patents or pending patent applications; see www.kaleo.com for details. KALÉO®and AUVI-Q®are registered trademarks of kaleo, Inc.
© 2024 kaleo, Inc.

*For California Only: This product uses batteries containing Perchlorate Material – special handling may apply. See www.dtsc.ca.gov/hazardouswaste/perchlorate

PATIENT INFORMATION

AUVI-Q® [Aw-Vee-Kyoo] (epinephrine injection)
Auto-Injector
For allergic emergencies (anaphylaxis)

Read this Patient Information Leaflet before you have to use AUVI-Q and each time you get a refill. There may be new information. You should know how to use AUVI-Q before you have an allergic emergency. This information does not take the place of talking with your healthcare provider about your medical condition or your treatment.

What is the most important information I should know about AUVI-Q?

1. Always carry AUVI-Q with you because you may not know when a life-threatening allergic reaction (anaphylactic reaction) may happen. Talk to your doctor if you need additional units to keep at work, school, etc. An anaphylactic reaction is a life-threatening allergic reaction that can happen within minutes and can be caused by stinging and biting insects (bees, wasps, hornets, and mosquitoes), allergy shots, foods, medicines, exercise, or other unknown causes. Follow your healthcare provider’s instructions on when to use AUVI-Q if you have the symptoms of an anaphylactic reaction, which may include the symptoms listed below:
  - trouble breathing
  - wheezing
  - hoarseness (changes in the way your voice sounds)
  - hives (raised reddened rash that may itch)
  - severe itching
  - swelling of your face, lips, mouth or tongue
  - skin rash, redness, or swelling
  - fast heartbeat
  - weak pulse
  - feeling very anxious
  - confusion
  - stomach pain
  - losing control of urine or bowel movements
  - dizziness or fainting
2. Tell your family members and others where you keep AUVI-Q and how to use it before you need it. You may be unable to speak in an allergic emergency.
3. Get medical attention immediately after using AUVI-Q. If you have a serious allergic reaction, you may need more medicine.

What is AUVI-Q?

AUVI-Q is a prescription medicine used to treat life-threatening allergic reactions including anaphylaxis in people who are at risk for or have a history of serious allergic reactions.

AUVI-Q is for immediate self (or caregiver) administration and does not take the place of emergency medical care. You should get emergency medical help right away after using AUVI-Q.

It is not known if AUVI-Q is safe and effective in children who weigh less than 16.5 pounds (7.5 kg).

What should I tell my healthcare provider before using AUVI-Q?
Before you use AUVI-Q, tell your healthcare provider if you:

- have heart problems or high blood pressure
- have diabetes
- have thyroid problems
- have history of depression
- have Parkinson’s disease
- have any other medical conditions
- are pregnant or plan to become pregnant. It is not known if AUVI-Q will harm your unborn baby.
- are breastfeeding or plan to breastfeed. It is not known if AUVI-Q passes into your breast milk.

Tell your healthcare provider about all the medicines you take,
including prescription and non-prescription medicines, vitamins, and herbal supplements.

AUVI-Q and other medicines may affect each other, causing side effects. AUVI-Q may affect the way other medicines work, and other medicines may affect how AUVI-Q works.

Know the medicines you take. Keep a list of them to show your healthcare provider and pharmacist when you get a new medicine.

How should I use AUVI-Q?

- Each AUVI-Q contains only 1 dose of medicine.
- AUVI-Q should only be injected into the muscle of your outer thigh. It can be injected through your clothing, if needed.
- Read the Instructions for Use at the end of this Patient Information Leaflet for information about the right way to use AUVI-Q.
- Use AUVI-Q exactly as your healthcare provider tells you to use it.
- You may request a Trainer for AUVI-Q. Additional training resources are available at www.auvi-q.com.
  - Practice with the Trainer for AUVI-Q before an allergic emergency happens to familiarize yourself with the use of AUVI-Q in an allergic emergency.
  - The Trainer for AUVI-Q does not contain a needle or medicine and can be reused to practice your injection.

What are the possible side effects of AUVI-Q?

AUVI-Q may cause serious side effects.

- AUVI-Q should only be injected into your outer thigh. Do notinject AUVI-Q into your:
  - veins
  - buttocks
  - fingers, toes, hands or feet
  If you accidentally inject AUVI-Q into any other part of your body, go to the nearest hospital emergency room right away. Tell the healthcare provider where on your body you received the accidental injection.
  - Rarely, patients who use AUVI-Q may develop infections at the injection site within a few days of an injection. Some of these infections can be serious. Call your healthcare provider right away if you have any of the following at an injection site:
    - redness that does not go away
    - swelling
    - tenderness
    - the area feels warm to the touch
  - If you inject a young child or infant with AUVI-Q, hold their leg firmly in place before and during the injection to prevent injuries. Ask your healthcare provider to show you how to properly hold the leg of a young child or infant during an injection.
- If you have certain medical conditions, or take certain medicines, your condition may get worse or you may have more or longer lasting side effects when you use AUVI-Q. Talk to your healthcare provider about all your medical conditions.

Common side effects of AUVI-Q include:

- fast, irregular, or ‘pounding’ heart beat
- sweating
- shakiness
- headache
- paleness
- feelings of over excitement, nervousness, or anxiety
- weakness
- dizziness
- nausea and vomiting
- breathing problems

Tell your healthcare provider if you have any side effect that bothers you or that does not go away.

These are not all of the possible side effects of AUVI-Q. For more information, ask your healthcare provider or pharmacist.

Call your doctor for medical advice about side effects. You may report side effects to FDA at 1-800-FDA-1088.

How should I store AUVI-Q?

- Store AUVI-Q at 68° to 77°F (20° to 25°C).
- Do NOT freeze. Do NOT expose to extreme heat or cold. For example, do NOT store in your vehicle’s glove box.
- Examine contents in the viewing window periodically. Solution should be clear. If the solution is discolored (pinkish color or darker than slightly yellow), cloudy or contains solid particles, replace the unit.
- Your AUVI-Q has an expiration date. Replace it before the expiration date.
- Keep AUVI-Q in the outer case it comes in to protect it from light.

Keep AUVI-Q and all medicines out of the reach of children.

General information about the safe and effective use of AUVI-Q:

Medicines are sometimes prescribed for purposes other than those listed in a Patient Information Leaflet. Do not use AUVI-Q for a condition for which it was not prescribed. Do not give AUVI-Q to other people, even if they have an allergic reaction or the same symptoms that you have. It may harm them.

This Patient Information Leaflet summarizes the most important information about AUVI-Q. If you would like more information, talk to your healthcare provider. You can ask your pharmacist or healthcare provider for information about AUVI-Q that is written for health professionals.

For more information and video instructions on the use of AUVI-Q, go to www.auvi-q.comor call 1-877-302-8847.

What are the ingredients in AUVI-Q?
Active ingredient: epinephrine.
Inactive Ingredients:sodium chloride, sodium bisulfite, hydrochloric acid, and water.

AUVI-Q does not contain latex.

Instructions for Use

Read these Instructions for Use carefully before you need to use your AUVI-Q. Before you use AUVI-Q, make sure your healthcare provider shows you the right way to use it. If you have any questions, ask your healthcare provider.

If you are administering AUVI-Q to a young child or infant, hold the leg firmly in place and limit movement prior to and while administering an injection.

Automated Voice Instructions

AUVI-Q contains an electronic voice instruction system to help guide you through each step of your injection. If the voice instructions do not work for any reason, use AUVI-Q as instructed in these Instructions for Use. It will still work during an allergic reaction emergency.

How to use your AUVI-Q

Figure A.

1. Pull AUVI-Q up from the outer case. See Figure B.
Do not go to step 2 until you are ready to use AUVI-Q. If you are not ready to use AUVI-Q, put it back in the outer case.

Figure B.

2. Pull Red safety guard down and off of AUVI-Q. See Figure C.
To reduce the chance of an accidental injection, do not touch the black base of the auto-injector, which is where the needle comes out. If an accidental injection happens, get medical help right away.

Note:The red safety guard is made to fit tight. Pull firmly to remove.

Figure C.

3. Place black end of AUVI-Q against the middle of the outer thigh (through clothing, if needed), then push firmly until you hear a click and hiss sound, and hold in place for 2 seconds. See Figure D.

Onlyinject into the middle of the outer thigh. Do notinject into any other part of the body.

If you are administering AUVI-Q to a young child or infant, hold the leg firmly in place while administering an injection See Figure E.

Figure D.

(For AUVI-Q 0.3 mg and AUVI-Q 0.15 mg)

Figure E.

(For AUVI-Q 0.1 mg)

Note:AUVI-Q makes a distinct sound (click and hiss) when you push it against your outer thigh. This is normal and indicates AUVI-Q is working correctly. Do not pull AUVI-Q away from your leg when you hear the click and hiss sound.

The needle automatically retracts after the injection is complete, so the needle will not be visible after the injection. AUVI-Q includes a 2-second countdown after it is activated, then the voice instruction will indicate the injection is complete, and to seek emergency medical attention, AUVI-Q will beep, and the lights will blink red.

4. Get emergency medical help right away.

Replace the outer case and talk to your healthcare provider about the right way to throw away your AUVI-Q.

Ask your healthcare provider for an AUVI-Q prescription refill.
After the use of AUVI-Q:

- The black base will lock into place.
- The voice instruction system will say “seek emergency medical attention”, say “this AUVI-Q has been used…”, and the lights will blink red.
- Do not replace the red safety guard.
- The viewing window will no longer be clear.
- It is normal for some medicine to remain in your AUVI-Q after you have received your dose of medicine.
- Talk to your healthcare provider about the right way to throw away your AUVI-Q.
- AUVI-Q is a single-dose auto-injector and cannot be reused. AUVI-Q must be used or properly disposed once the red safety guard is removed.

Until you throw away your used AUVI-Q, the electronic voice instruction system will remind you that it has been used when the outer case is removed.

If you will be administering AUVI-Q to a young child or infant, ask your healthcare provider to show you how to properly hold the leg in place while administering a dose.

This Patient Information has been approved by the U.S. Food and Drug Administration.

Rev. Feb 2024

Manufactured for:
kaleo, Inc.
Richmond, VA 23219 USA
This product may be covered by one or more U.S. patents or pending patent applications; see www.kaleo.comfor details. KALÉO® and AUVI-Q® are registered trademarks of kaleo, Inc.
© 2024 kaleo, Inc.

*For California Only: This product uses batteries containing Perchlorate Material – special handling may apply. See www.dtsc.ca.gov/hazardouswaste/perchlorate

TRAINER FOR AUVI-Q® Trainer Instructions for Use

Important:
The TRAINER for AUVI-Q Does Not contain a needle or medicine.

In case of an allergic emergency, use the real AUVI-Q and not the gray Trainer.
Always carry your real Auvi-Q with you in case of an allergic emergency.

Important Information about the TRAINER for AUVI-Q:

Inside your TRAINER for AUVI-Q are:

- batteries
- a speaker that will make a beeping sound and that produces electronic voice instructions
- red and green blinking lights

The TRAINER for AUVI-Q batteries are made to last long enough for you to practice 1 time each day for 2 years. If your TRAINER for AUVI-Q does not work properly call your healthcare provider for a new Trainer.

What is the TRAINER for AUVI-Q?

- The TRAINER for AUVI-Q does not contain a needle or medicine and can be reused to practice your injection.
- Practice with the TRAINER for AUVI-Q before an allergic emergency happens to make sure you are able to safely use the real AUVI-Q in an emergency.

Your TRAINER for AUVI-Q
Figure A

TRAINER for AUVI-Q
Top view

AUVI-Q
AUVI-Q 0.3 mg is orange
AUVI-Q 0.15 mg is blue
AUVI-Q 0.1 mg is white and lavender

TRAINER for AUVI-Q:

- is inside a gray outer case
- does not have a needle or medicine inside
- can be reused (the red safety guard can be placed back on the base of the Trainer after use)
- has no expiration date
- has embossed “TRAINER” on top of the device

AUVI-Q:

- is inside an orange (0.3 mg)or blue (0.15 mg)or white and lavender (0.1 mg) outer case
- contains a needle and epinephrine medicine
- cannot be reused(AUVI-Q must be used or properly disposed once the red safety guard is removed)
- has a medicine expiration date listed on the device

In case of an allergic emergency, use the real AUVI-Q and notthe gray Trainer.

Who should practice using the TRAINER for AUVI-Q?
Anyone who may need to help you with AUVI-Q in case of an allergic emergency:

- You
- Caregivers
- Family
- Friends
- Co-workers
- Teachers
- Child Care or Day Care Workers

Have them practice using the Trainer and review the Patient Information Leaflet included in the packaging with each prescription of AUVI-Q.
For more information and video instructions on the use of AUVI -Q, go to www.AUVI-Q.comor call 1-877-302-8847.

Practicing with the TRAINER for AUVI-Q
Practice with the TRAINER for AUVI-Q before an allergic emergency happens to make sure you are able to safely use the real AUVI-Q in an emergency.

- You should practice daily for the first week after you receive your TRAINER for AUVI-Q to help you feel comfortable using AUVI-Q quickly and safely. Even when you are comfortable using the Trainer, continue to practice using it often.

How to Use the Trainer

How the TRAINER for AUVI-Q works
Although the Trainer does not have a needle and contains no medicine, it works the same way as the real AUVI-Q.
As with the real AUVI-Q, the TRAINER for AUVI-Q contains an electronic voice instruction system to help guide you through each step of your injection. If the voice instructions do not work for the TRAINER for AUVI-Q for any reason, you can still use the TRAINER for AUVI-Q as instructed in this leaflet to practice.
The TRAINER for AUVI-Q has the same blinking red and green lights as the real AUVI-Q.
As with the real AUVI-Q, if practicing with a young child or infant, hold the leg firmly in place while using the TRAINER for AUVI-Q. Ask your healthcare provider to show you how to properly hold the leg to practice so that you will be prepared before an allergic emergency happens.

Follow These Steps

1.Pull the TRAINER for AUVI-Q from the outer case.See Figure B

2. Pull Red safety guard down and off of the Trainer.See Figure C.

Figure B

Figure C

Note: The red safety guard is made to fit tight similar to the safety guard on the real AUVI-Q. Pull firmly to remove.

3. Place black end against the middle of the outer thigh (through clothing, if needed), then push firmly until you hear a click and hiss sound, and hold in place for 2 seconds.See Figure D.
As with the real AUVI-Q, if practicing with a young child or infant, hold the leg firmly in place while using the TRAINER for AUVI-Q.(See Figure E).

Figure D

Figure E

Note: In an actual emergency, after the injection you would need to seek medical help right away.
Onlypractice using the middle of your outer thigh. The outer thigh is where you would inject with the real AUVI-Q.
Note: The TRAINER for AUVI-Q makes a distinct sound (click and hiss) when you push it firmly against your outer thigh. This is the same sound that is made with the real AUVI-Q. This is normal, and indicates AUVI-Q is working correctly. Do not pull AUVI-Q away from your leg when you hear the click and hiss sound.

4. After practicing, reset the TRAINER for AUVI-Q:
a. Replace the Red safety guard.Do not hold the black base while inserting the Red safety guard. The Black base will drop down into its original location during Red safety guard insertion. See Figure F.
b. Slide the TRAINER for AUVI-Q all the way back into the gray outer case to reset the electronic voice system.See Figure G.

Figure F

Figure G

Note: Leave the TRAINER for AUVI-Q in its outer case for at least 5 seconds between each time you practice to allow the electronic voice system to reset.

Storage:

- Store the TRAINER for AUVI-Q at room temperature; the TRAINER for AUVI-Q should not be used at temperatures less than 50°F (10°C) or greater than 104°F (40°C).
- Store the TRAINER for AUVI-Q in its outer case.
- Keep the TRAINER for AUVI-Q away from dirt, chemicals, and water.

Disposal:
The TRAINER for AUVI-Q contains electronics and lithium coin cell batteries, and should be disposed of in the correct manner. Follow your State and local environmental regulations for disposal.

For California Only: This product uses batteries containing Perchlorate Material - special handling may apply. See www.dtsc.ca.gov/hazardouswaste/perchlorate

Manufactured for:
kaleo, Inc.
Richmond, VA 23219 USA

This product may be covered by one or more U.S. patents or pending patent applications; see www.kaleo.comfor details. KALÉO® and AUVI-Q® are registered trademarks of kaleo, Inc.
© 2024 kaleo, Inc.

Rev. Feb 2024

PRINCIPAL DISPLAY PANEL - OUTER PACKAGE

NDC 71872-7333-1

Auvi-Q epinephrine Injection, USP

0.15mg

1 x prefilled auto-injector

RX Only